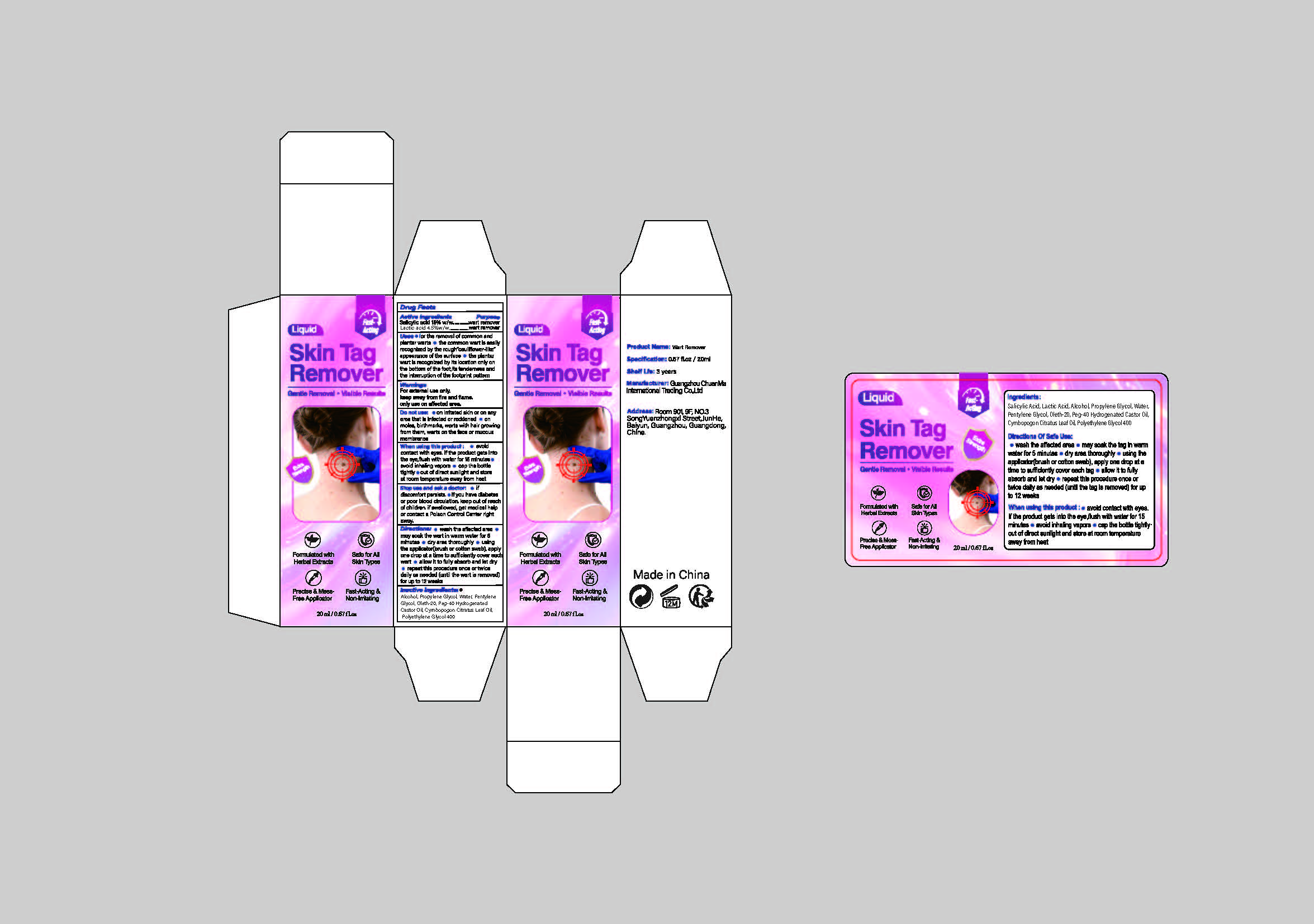 DRUG LABEL: SKIN TAG REMOVER
NDC: 85593-102 | Form: LIQUID
Manufacturer: Guangzhou ChuanMa International Trading Co.,Ltd.
Category: otc | Type: HUMAN OTC DRUG LABEL
Date: 20250720

ACTIVE INGREDIENTS: LACTIC ACID 4.5 g/100 mL; SALICYLIC ACID 15 g/100 mL
INACTIVE INGREDIENTS: PROPYLENE GLYCOL; OLETH-20; POLYETHYLENE GLYCOL 400; ALCOHOL; PEG-40 HYDROGENATED CASTOR OIL; CYMBOPOGON CITRATUS LEAF OIL; WATER; PENTYLENE GLYCOL

ACTIVE INGREDIENT

Active ingredrentsSalicylic acid 15% w/w....Lactic acid 4.5%w/w.

PURPOSE

Skin TagRemover
Gentle Removal ·Visible Results

DO NOT USE

on irritated skin or on anyarea that is infected or reddened e onmoles, birthmarks, warts with hair growingfrom them, warts on the face or mucousmembranes

WARNINGS

WarningsFor external use only.keep away from fire and flame.only use on affected area.

INDICATIONS AND USAGE

for the removal of common andplantar warts ● the common wart is easilyrecognized by the rough"cauliflower-likeappearance of the surface ● the plantarwart is recognized by its location only onthe bottom of the foot,its tenderness andthe interruption of the footprint pattern

DOSAGE AND ADMINISTRATION

wash the affected areamay soak the wart in warm water for 5minutes o dry area thoroughly o usingthe applicator(brush or cotton swab), applyone drop at a time to sufficiently cover eachwart e allow it to fully absorb and let dryrepeat this procedure once or twicedaily as needed (until the wart is removed)for up to 12 weeks

KEEP OUT OF REACH OF CHILDREN

keep out of reachof children, if swallowed, get medical helpor contact a Poison Control Center rightaway

INACTIVE INGREDIENT

Inactive ingredients:®Alcohol, Propylene Glycol, Water, PentyleneGlycol, Oleth-20, Peg-40 HydrogenatedCastor Oil, Cymbopogon Citratus Leaf Oil,Polyethylene Glycol 400